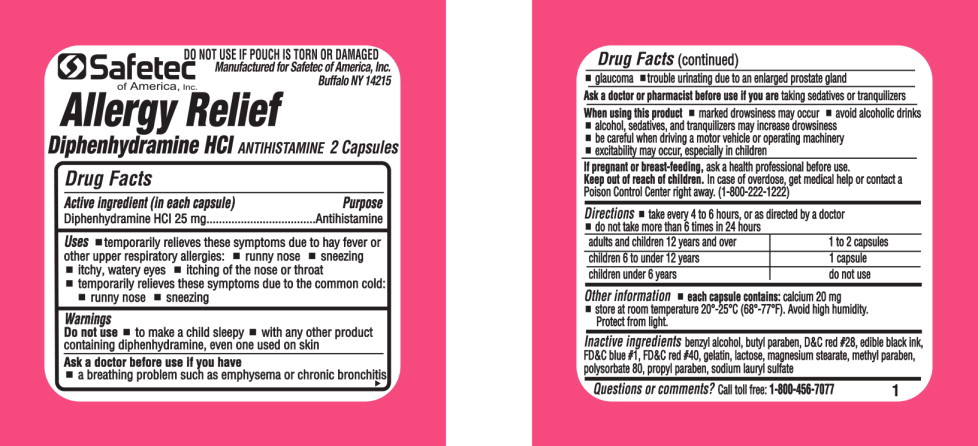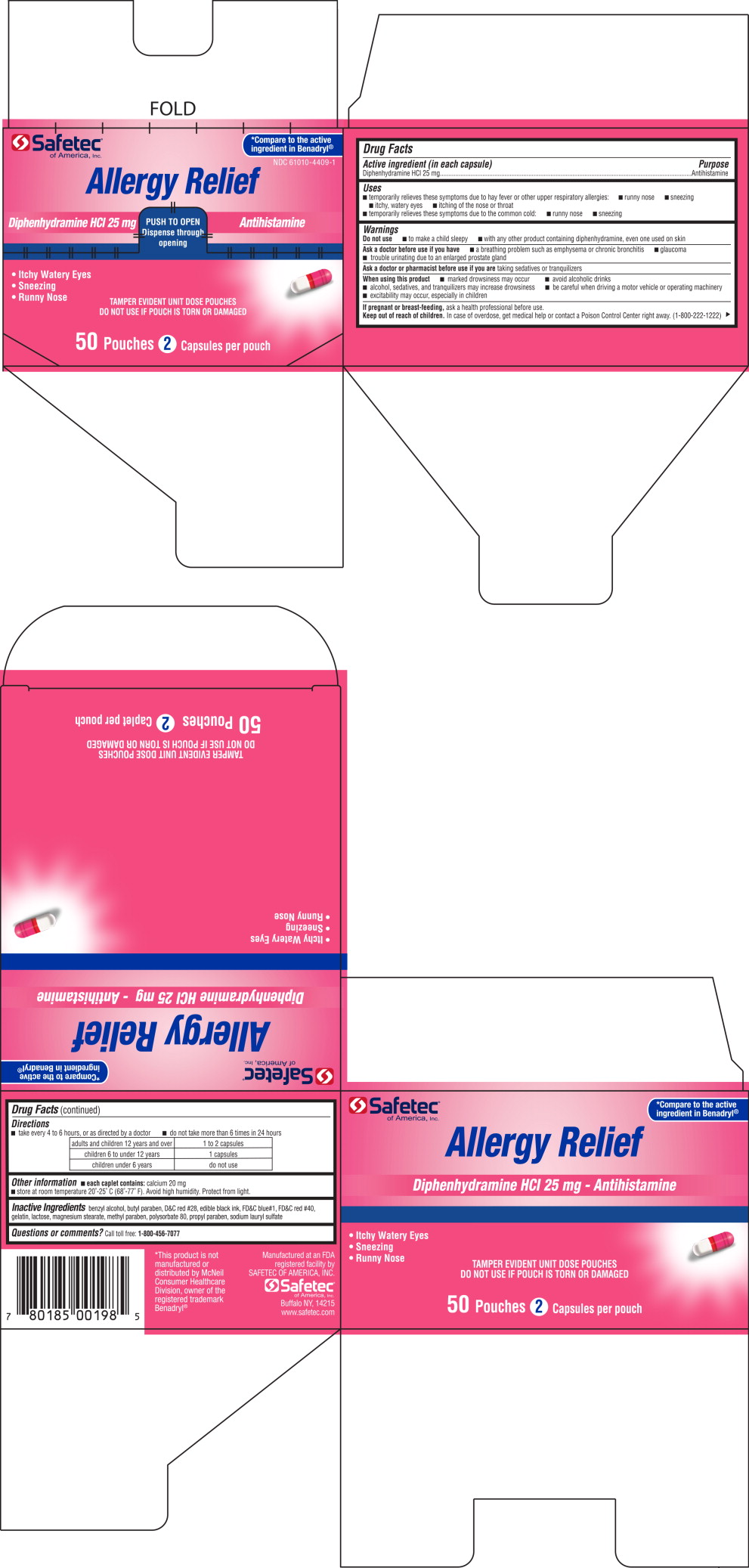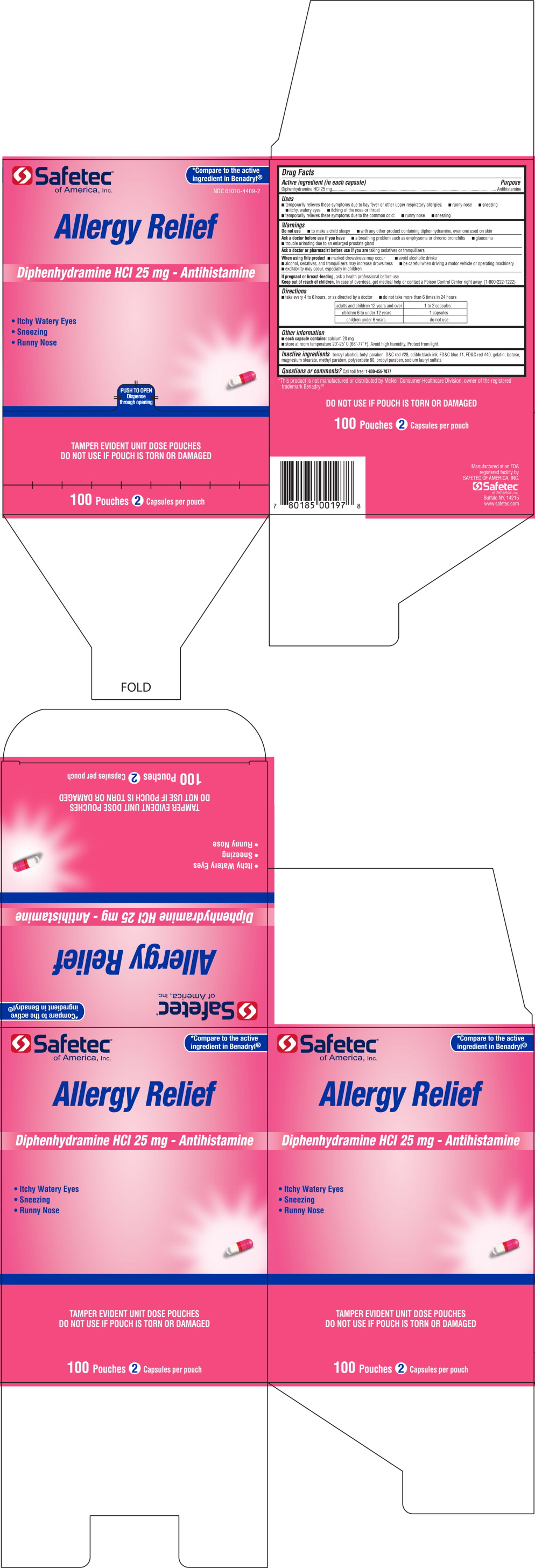 DRUG LABEL: Diphenhydramine
NDC: 61010-4409 | Form: CAPSULE
Manufacturer: Safetec of America, Inc.
Category: otc | Type: HUMAN OTC DRUG LABEL
Date: 20200127

ACTIVE INGREDIENTS: Diphenhydramine Hydrochloride 25 mg/1 1
INACTIVE INGREDIENTS: benzyl alcohol; butylparaben; D&C red NO. 28; FD&C BLUE NO. 1; FD&C RED NO. 40; GELATIN; LACTOSE, UNSPECIFIED FORM; MAGNESIUM STEARATE; METHYLPARABEN; POLYSORBATE 80; PROPYLPARABEN; SODIUM LAURYL SULFATE

Drug Facts

Active ingredient (in each capsule)

Diphenhydramine HCl 25 mg

Purpose

Antihistamine

Uses

- temporarily relieves these symptoms due to hay fever or other upper respiratory allergies:
  - runny nose
  - sneezing
  - itchy, watery eyes
  - itching of the nose or throat
  - temporarily relieves these symptoms due to the common cold:
  - runny nose sneezing

Warnings

Do not use

- to make a child sleepy
- with any other product containing diphenhydramine, even one used on skin

Ask a doctor before use if you have

- a breathing problem such as emphysema or chronic bronchitis
- glaucoma
- trouble urinating due to an enlarged prostate gland

When using this product

- marked drowsiness may occur
- avoid alcoholic drinks
- alcohol, sedatives, and tranquilizers may increase drowsiness
- be careful when driving a motor vehicle or operating machinery
- excitability may occur, especially in children

If pregnant or breast-feeding, ask a health professional before use.

Keep out of reach of children. In case of overdose, get medical help or contact a Poison Control Center right away. (1-800-222-1222)

Directions

- take every 4 to 6 hours, or as directed by a doctor
- do not take more than 6 times in 24 hours

adults and children 12 years and over | 1 to 2 capsules
children 6 to under 12 years | 1 capsule
children under 6 years | do not use

Other information

- each capsule contains: calcium 20 mg
- store at room temperature 20°-25°C (68°-77°F). Avoid high humidity. Protect from light

Inactive ingredients

benzyl alcohol, butyl paraben, D&C red #28, edible black ink, FD&C blue #1, FD&C red #40, gelatin, lactose, magnesium stearate, methyl paraben, polysorbate 80, propyl paraben, sodium lauryl sulfate

Questions or comments?

Call toll free: 1-800-456-7077

Principal Display Panel - 25 mg Pouch Label

Safetec
of America, Inc.

DO NOT USE IF POUCH IS TORN OR DAMAGED

Manufactured for Safetec of America, Inc.
Buffalo NY 14215

Allergy Relief

Diphenhydramine HCl

antihistamine 2 Capsules

Principal Display Panel – 50 Pouches Carton Label

Safetec®
of America, Inc.

*Compare to the active ingredient in Benadryl®

NDC 61010-4409-1

Allergy Relief

Diphenhydramine HCl 25 mg

PUSH TO OPEN

Dispense through opening

Antihistamine

- Itchy Watery Eyes
- Sneezing
- Runny Nose

TAMPER EVIDENT UNIT DOSE POUCHES

DO NOT USE IF POUCH IS TORN OR DAMAGED

50 Pouches 2 Capsules per pouchGraphic-Untitled

Principal Display Panel – 100 Pouches Carton Label

Safetec®
of America, Inc.

*Compare to the active ingredient in Benadryl®

NDC 61010-4409-2

Allergy Relief

Diphenhydramine HCl 25 mg – Antihistamine

- Itchy Watery Eyes
- Sneezing
- Runny Nose

PUSH TO OPEN

Dispense through opening

TAMPER EVIDENT UNIT DOSE POUCHES

DO NOT USE IF POUCH IS TORN OR DAMAGED

100 Pouches 2 Capsules per pouch